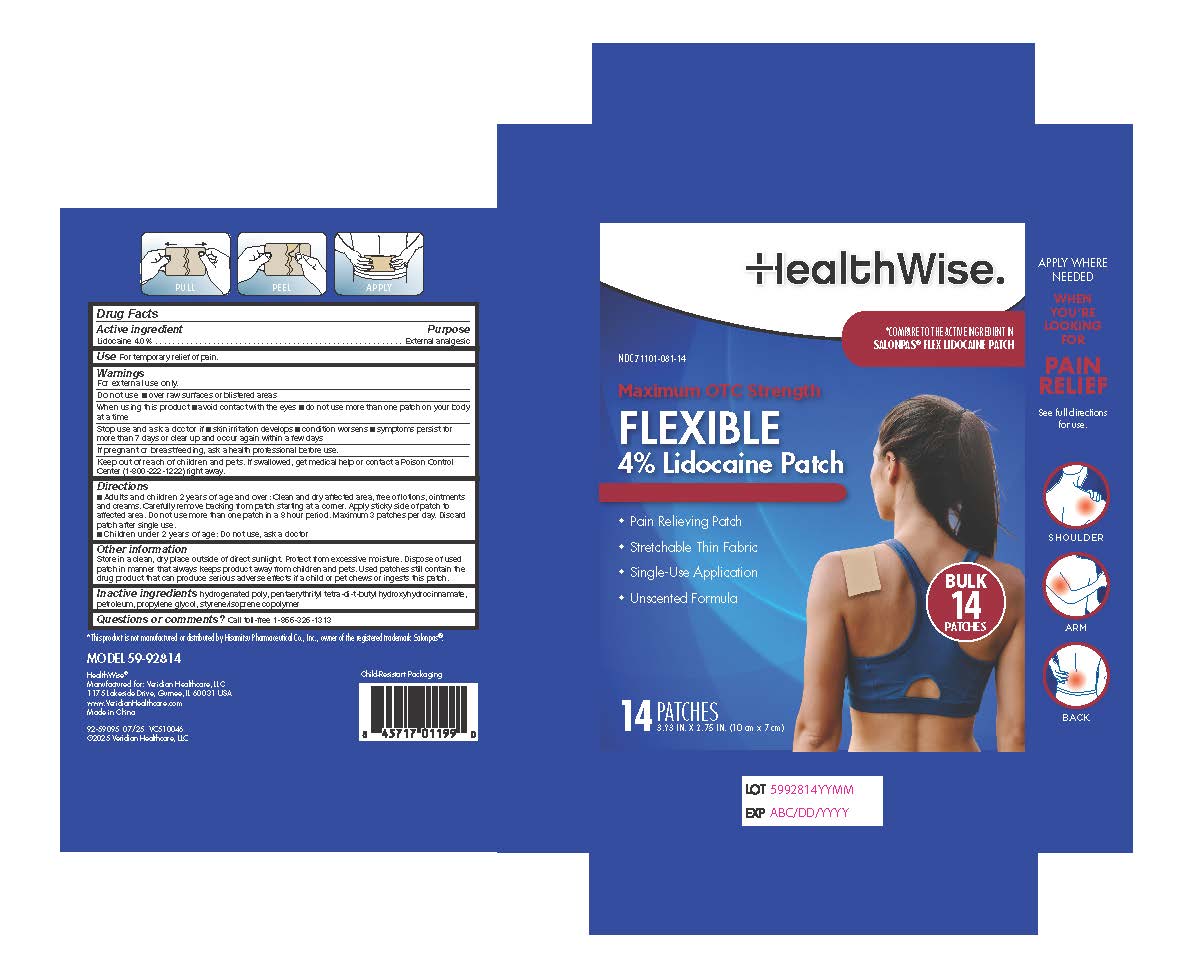 DRUG LABEL: HealthWise Flexible 4% Lidocaine Patch
NDC: 71101-081 | Form: PATCH
Manufacturer: Veridian Healthcare
Category: otc | Type: HUMAN OTC DRUG LABEL
Date: 20250722

ACTIVE INGREDIENTS: LIDOCAINE 4 g/100 g
INACTIVE INGREDIENTS: HYDROGENATED C6-20 POLYOLEFIN (100 CST); PENTAERYTHRITOL TETRAKIS(3-(3,5-DI-TERT-BUTYL-4-HYDROXYPHENYL)PROPIONATE); LIQUID PETROLEUM; STYRENE/ISOPRENE COPOLYMER (28:72; 210000 MW); PROPYLENE GLYCOL

HealthWise Flexible 4% Lidocaine Patch

Active Ingredient

Lidocaine 4.0%

Purpose

External analgesic

Use

Temporarily relief of pain.

Warnings

For External Use Only

Do not use

■over raw surfaces or blistered areas

When using this product

■ Avoid contact with the eyes

■ Do not use more than one patch on your body at a time

Stop use and consult a doctor if

■ skin Irritation develops

■ Condition worsens

■ Symptoms persist for more than 7 days or clear up and occur again within a few days

PREGNANCY OR BREAST FEEDING

If pregnant or breastfeeding, ask a health professional before use.

Keep out of reach of children and pets.

If swallowed, get medical help or contact a Poison Control Center (1-800-222-1222) right away.

Directions

■ Adults and children 2 years of age and over: Clean and dry affected area, free of lotions, ointments and creams. Carefully remove backing from patch starting at a corner. Apply sticky side of patch to affected area. Do not use more than one patch in a 8 hour period. Maximum 3 patches per day. Discard patch after single use.
■ Children under 2 years of age: Do not use, ask a doctor

Other Information

Store in a clean, dry place outside of direct sunlight. Protect from excessive moisture. Dispose of used patch in manner that always keeps product away from children and pets. Used patches still contain the drug product that can produce serious adverse effects if a child or pet chews or ingests this patch.

Inactive Ingredients

hydrogenated poly, pentaerythrityl tetra-di-t-butyl hydroxyhydrocinnamate, petroleum, propylene glycol, styrene/isoprene copolymer